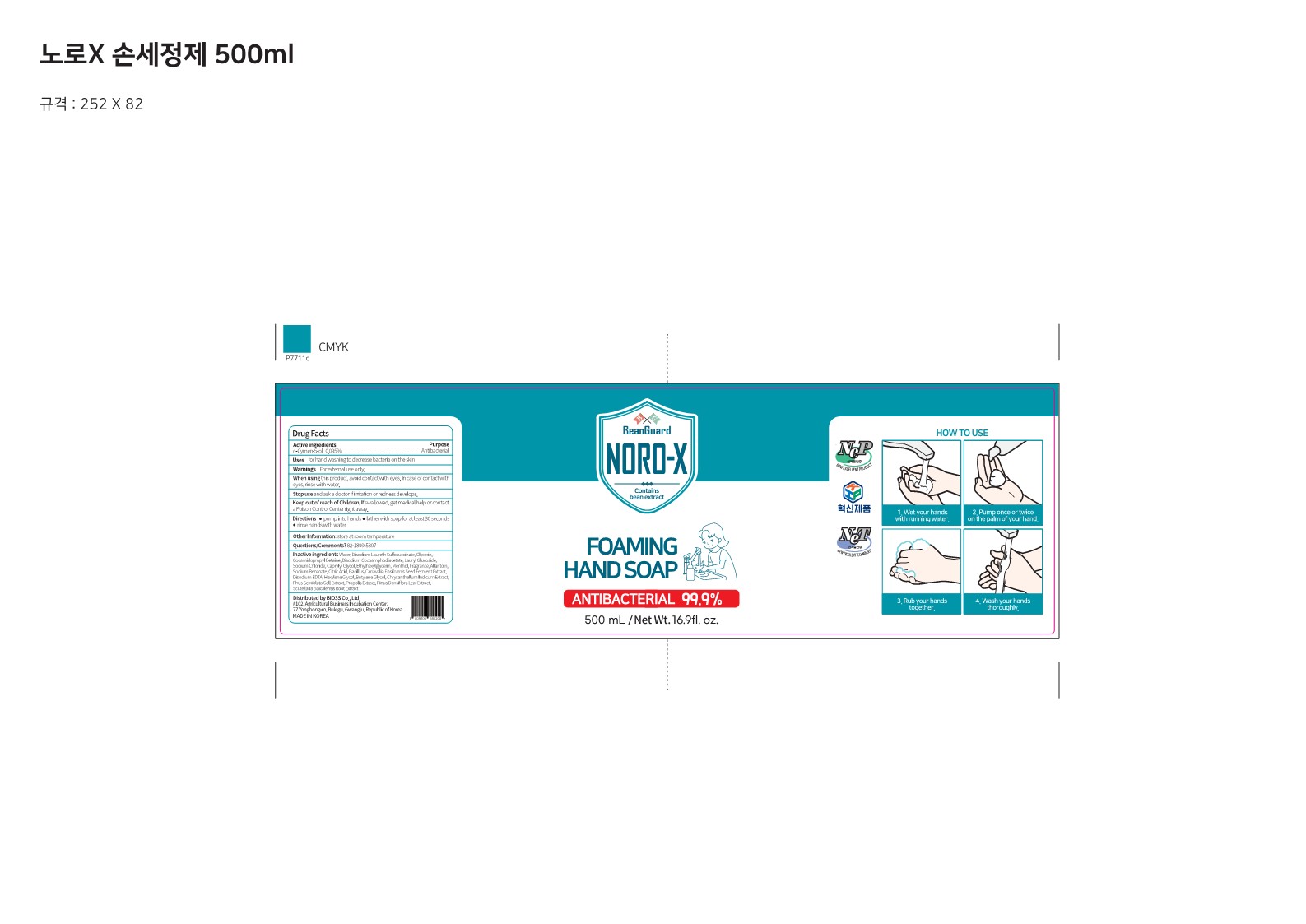 DRUG LABEL: NORO-X Foaming HandSoap
NDC: 77935-507 | Form: SOAP
Manufacturer: BIO3S Co.,Ltd.
Category: otc | Type: HUMAN OTC DRUG LABEL
Date: 20230221

ACTIVE INGREDIENTS: O-CYMEN-5-OL 0.095 g/100 mL
INACTIVE INGREDIENTS: DISODIUM LAURETH SULFOSUCCINATE; COCAMIDOPROPYL BETAINE; LAURYL GLUCOSIDE; ETHYLHEXYLGLYCERIN; SODIUM BENZOATE; EDETATE DISODIUM ANHYDROUS; CHRYSANTHELLUM INDICUM TOP; MENTHOL; ALLANTOIN; CITRIC ACID MONOHYDRATE; CAPRYLYL GLYCOL; BUTYLENE GLYCOL; PINUS DENSIFLORA LEAF; HEXYLENE GLYCOL; FRAGRANCE CLEAN ORC0600327; GLYCERIN; WATER; DISODIUM COCOAMPHODIACETATE; PROPOLIS WAX; SCUTELLARIA BAICALENSIS ROOT; RHUS CHINENSIS GALL; CANAVALIA ENSIFORMIS WHOLE; SODIUM CHLORIDE

77935-507 NORO-X Foaming Hand Soap 500mL

Active ingredients

o-Cymen-5-ol 0.095%

Purposes

o-Cymen-5-ol 0.095%............................................ Antibacterial

Uses

Uses for hand washing to decrease bacteria on the skin

Warnings

Warnings For external use only.

Warnings

When using this product, avoid contact with eyes. In case of contact with eyes, rinse with water.

Warnings

Stop use and ask a doctor if irritation or redness develops.

Warnings

Keep out of reach of Children. If swallowed, get medical help or contact a Poison Control Center right away.

Directions

• pump into hands

• lather with soap for at least 30 seconds

• rinse hands with water

Inactive ingredients

Water, Disodium Laureth Sulfosuccinate, Glycerin, Cocamidopropyl Betaine, Disodium Cocoamphodiacetate, Lauryl Glucoside,
Sodium Chloride, Capiylyi Glycol, Ethyihexylglycerin, Menthol, Fragrance, Allantoin, Sodium Benzoate, Citric Acid, Bacillus/Canavalia Ensiformis Seed Ferment Extract, Disodium EDTA, Hexylene Glycol, Butylene Glycol, Chrysanthellum Indicum Extract,
RhusSemialata Gall Extract, Propolis Extract, Pinus Densiflora Leaf Extract, Scutellaria Baicalensis Root Extract